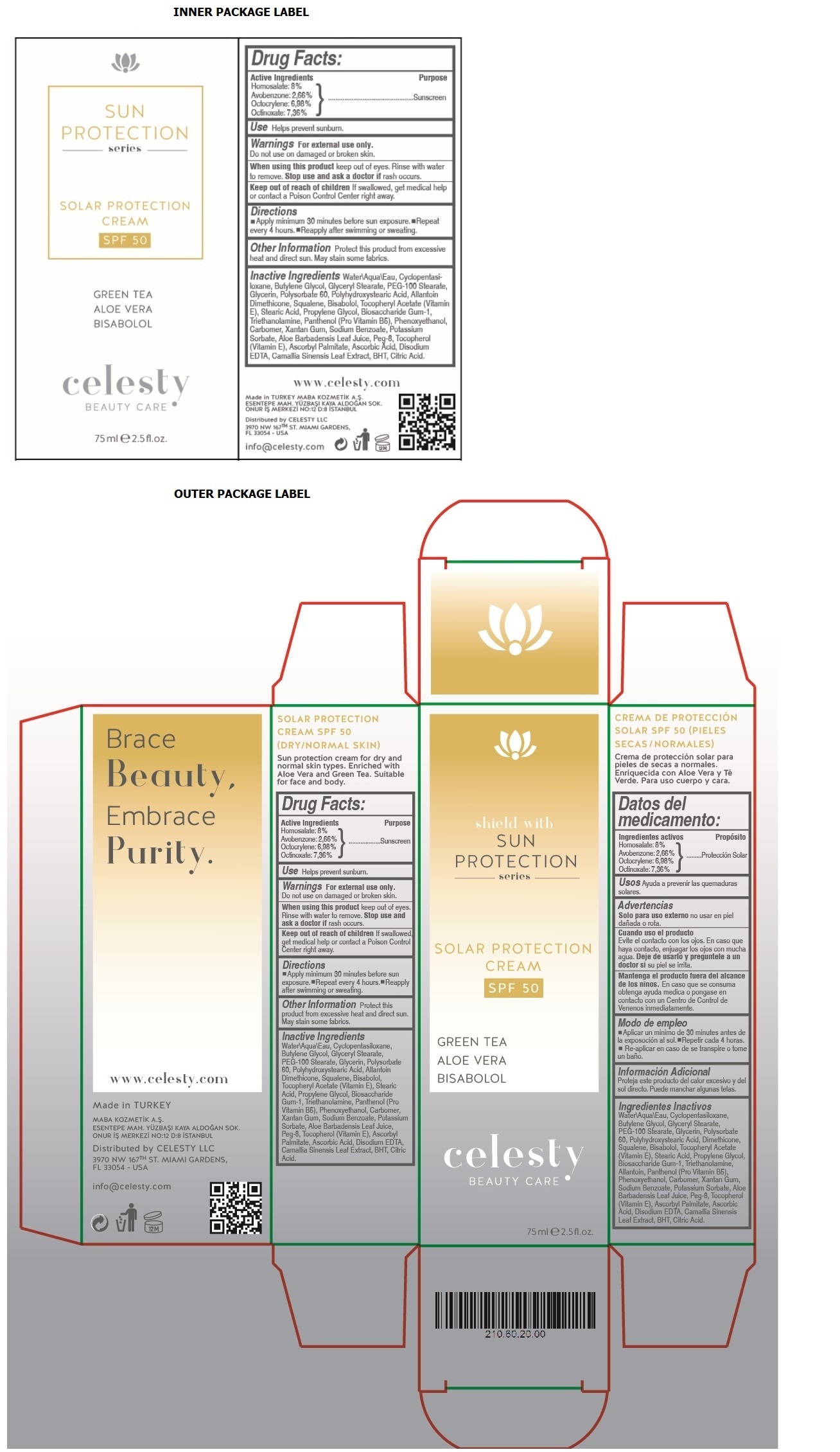 DRUG LABEL: Celesty
NDC: 81120-110 | Form: CREAM
Manufacturer: MABA KOZMETIK LIMITED SIRKETI
Category: otc | Type: HUMAN OTC DRUG LABEL
Date: 20201209

ACTIVE INGREDIENTS: HOMOSALATE 80 mg/1 mL; AVOBENZONE 26.6 mg/1 mL; OCTOCRYLENE 69.8 mg/1 mL; OCTINOXATE 73.6 mg/1 mL
INACTIVE INGREDIENTS: WATER; CYCLOMETHICONE 5; BUTYLENE GLYCOL; GLYCERYL MONOSTEARATE; PEG-100 STEARATE; GLYCERIN; POLYSORBATE 60; POLYHYDROXYSTEARIC ACID (2300 MW); ALLANTOIN; DIMETHICONE; SQUALENE; LEVOMENOL; .ALPHA.-TOCOPHEROL ACETATE; STEARIC ACID; PROPYLENE GLYCOL; BIOSACCHARIDE GUM-1; TROLAMINE; PANTHENOL; PHENOXYETHANOL; CARBOMER HOMOPOLYMER, UNSPECIFIED TYPE; XANTHAN GUM; SODIUM BENZOATE; POTASSIUM SORBATE; ALOE VERA LEAF; POLYETHYLENE GLYCOL 400; TOCOPHEROL; ASCORBYL PALMITATE; ASCORBIC ACID; EDETATE DISODIUM ANHYDROUS; GREEN TEA LEAF; BUTYLATED HYDROXYTOLUENE; CITRIC ACID MONOHYDRATE

Celesty SUN PROTECTION series SOLAR PROTECTION CREAM SPF 50

Active Ingredients

Homosalate: 8%

Avobenzone: 2,66%

Octocrylene: 6,98%

Octinoxate: 7,36%

Purpose

Sunscreen

Use

Helps prevent sunburn.

Warnings

For external use only.

Do not use on damaged or broken skin.

When using this product keep out eyes. Rinse with water to remove. Stop use and ask a doctor if rash occurs.

Keep out of reach of children If swallowed, get medical help or contact a Poison Control Center right away.

Directions

• Apply minimum 30 minutes before sun exposure. • Repeat every 4 hours. • Reapply after swimming or sweating.

Other Information

Protect this product from excessive heat and direct sun. May stain some fabrics.

Inactive Ingredients

Water\Aqua\Eau, Cyclopentasiloxane, Butylene Glycol, Glyceryl Stearate, PEG-100 Stearate, Glycerin, Polysorbate 60, Polyhydroxystearic Acid, Allantoin, Dimethicone, Squalene, Bisabolol, Tocopheryl Acetate (Vitamin E), Stearic Acid, Propylene Glycol, Biosaccharide Gum-1, Triethanolamine, Panthenol (Pro Vitamin B5), Phenoxyethanol, Carbomer, Xanthan Gum, Sodium Benzoate, Potassium Sorbate, Aloe Barbadensis Leaf Juice, Peg-8, Tocopherol (Vitamin E), Ascorbyl Palmitate, Ascorbic Acid, Disodium EDTA, Camallia Sinensis Leaf Extract, BHT, Citric Acid.

shield with

GREEN TEA

ALOE VERA

BISABOLOL

BEAUTY CARE

SOLAR PROTECTION CREAM SPF 50 (DRY/NORMAL SKIN)

Sun protection cream for dry and normal skin types. Enriched with Aloe Vera and Green Tea. Suitable for face and body.

Brace Beauty, Embrace Purity.

www.celesty.com

Made in TURKEY

MABA KOZMETIK A.S.

ESENTEPE MAH. YUZBASI KAYA ALDOGAN SOK.

ONUR IS MERKEZI NO:12 D:8 ISTANBUL

Distributed by CELESTY LLC

3970 NW 167TH ST. MIAMI GARDENS,

FL 33054 - USA

info@celesty.com